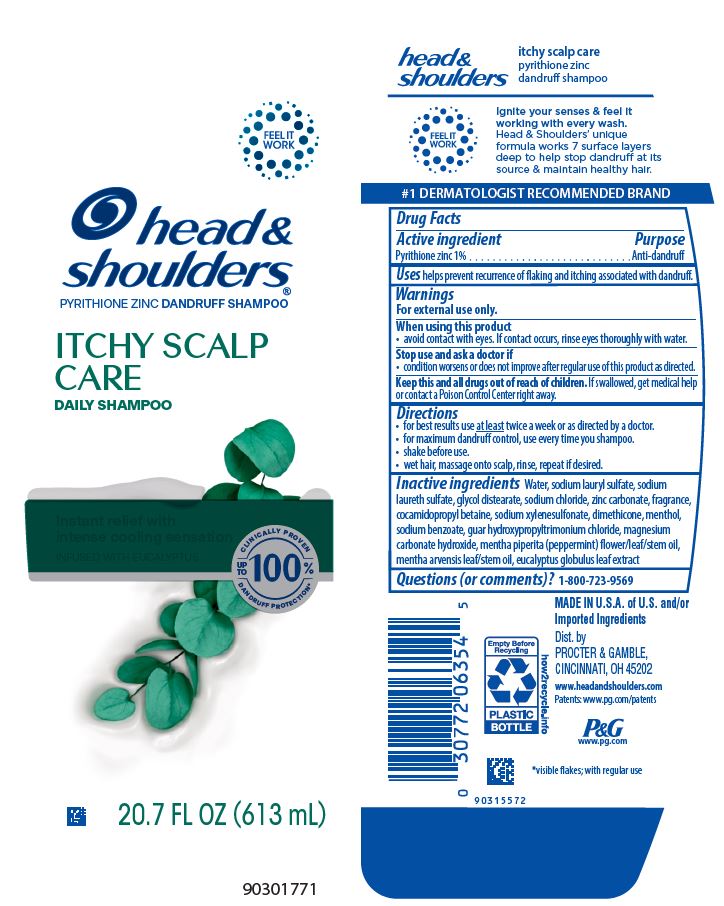 DRUG LABEL: Head and Shoulders
NDC: 37000-079 | Form: LOTION/SHAMPOO
Manufacturer: The Procter & Gamble Manufacturing Company
Category: otc | Type: HUMAN OTC DRUG LABEL
Date: 20251231

ACTIVE INGREDIENTS: PYRITHIONE ZINC 1 g/100 mL
INACTIVE INGREDIENTS: SODIUM CHLORIDE; SODIUM XYLENESULFONATE; COCAMIDOPROPYL BETAINE; DIMETHICONE; SODIUM BENZOATE; MAGNESIUM CARBONATE HYDROXIDE; EUCALYPTUS GLOBULUS LEAF; PEPPERMINT; MENTHOL, UNSPECIFIED FORM; MENTHA ARVENSIS LEAF OIL; GUAR HYDROXYPROPYLTRIMONIUM CHLORIDE (1.7 SUBSTITUENTS PER SACCHARIDE); WATER; SODIUM LAURYL SULFATE; SODIUM LAURETH-3 SULFATE; GLYCOL DISTEARATE; ZINC CARBONATE

Head and Shoulders®
Itchy Scalp

Drug Facts

Active ingredient

Pyrithione zinc 1%

Purpose

Anti-dandruff

Uses

helps prevent recurrence of flaking and itching associated with dandruff.

Warnings

For external use only.

When using this product

- avoid contact with eyes. If contact occurs, rinse eyes thoroughly with water.

Stop use and ask a doctor if

- condition worsens or does not improve after regular use of this product as directed.

KEEP OUT OF REACH OF CHILDREN

Keep this and all drugs out of reach of children. If swallowed, get medical help or contact a Poison Control Center right away.

Directions

- for best results use at least twice a week or as directed by a doctor.
- for maximum dandruff control, use every time you shampoo.
- shake before use.
- wet hair, massage onto scalp, rinse, repeat if desired.

Inactive ingredients

Water, sodium lauryl sulfate, sodium laureth sulfate, glycol distearate, sodium chloride, zinc carbonate, fragrance, cocamidopropyl betaine, sodium xylenesulfonate, dimethicone, menthol, sodium benzoate, guar hydroxypropyltrimonium chloride, magnesium carbonate hydroxide, mentha piperita (peppermint) flower/leaf/stem oil, mentha arvensis leaf/stem oil, eucalyptus globulus leaf extract

Questions (or comments)?

1-800-723-9569

Dist. by PROCTER & GAMBLE,
CINCINNATI, OH 45202

PRINCIPAL DISPLAY PANEL - 613 mL Bottle Label

head &
shoulders®

pyrithione zinc dandruff shampoo

ITCHY SCALP CARE

DAILY SHAMPOO

relieves scalp itch†

infused with eucalyptus

FLAKE FREE.*
UP TO 100%
GUARANTEED^

20.7 FL OZ (613 mL)